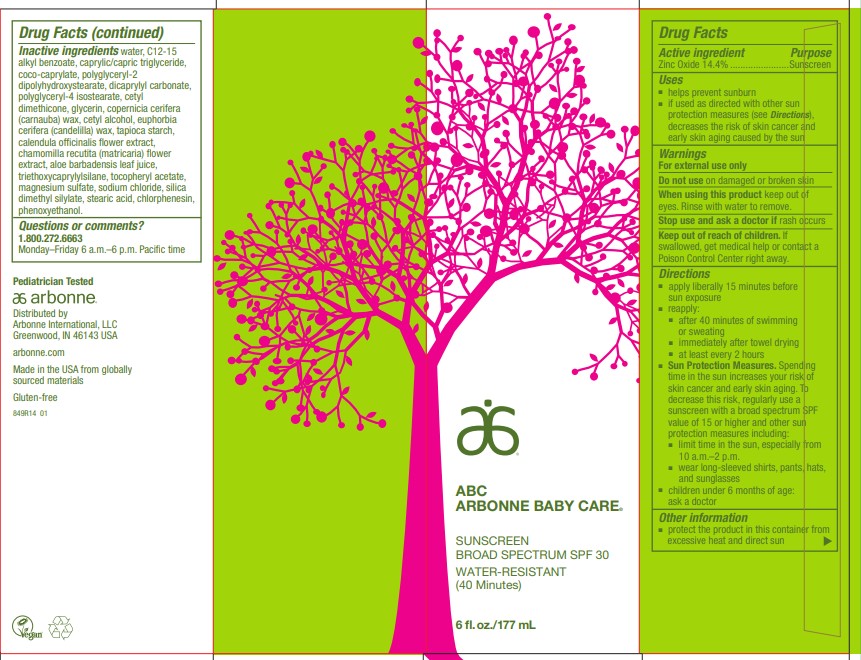 DRUG LABEL: ABC Arbonne Baby Care Sunscreen Broad Spectrum SPF 30 Water-Resistant (40 Minutes)
NDC: 42508-332 | Form: LOTION
Manufacturer: Arbonne International, LLC
Category: otc | Type: HUMAN OTC DRUG LABEL
Date: 20241112

ACTIVE INGREDIENTS: ZINC OXIDE 144 mg/1 mL
INACTIVE INGREDIENTS: WATER; ALKYL (C12-15) BENZOATE; MEDIUM-CHAIN TRIGLYCERIDES; COCO-CAPRYLATE; POLYGLYCERYL-2 DIPOLYHYDROXYSTEARATE; DICAPRYLYL CARBONATE; POLYGLYCERYL-4 ISOSTEARATE; CETYL DIMETHICONE 25; GLYCERIN; CARNAUBA WAX; CETYL ALCOHOL; CANDELILLA WAX; STARCH, TAPIOCA; CALENDULA OFFICINALIS FLOWER; CHAMOMILE; ALOE VERA LEAF; TRIETHOXYCAPRYLYLSILANE; .ALPHA.-TOCOPHEROL ACETATE; MAGNESIUM SULFATE, UNSPECIFIED FORM; SODIUM CHLORIDE; SILICA DIMETHYL SILYLATE; STEARIC ACID; CHLORPHENESIN; PHENOXYETHANOL

ABC Arbonne Baby Care®Sunscreen Broad Spectrum SPF 30 Water-Resistant (40 Minutes)

Drug Facts

Active ingredient

Zinc Oxide 14.4%

Purpose

Sunscreen

Uses

- helps prevent sunburn
- if used as directed with other sun protection measures (see Directions), decreases the risk of skin cancer and early skin aging caused by the sun

Warnings

For external use only

Do not useon damaged or broken skin

WHEN USING

When using this productkeep out of eyes. Rinse with water to remove.

Stop use and ask a doctor ifrash occurs

Keep out of reach of children.If swallowed, get medical help or contact a Poison Control Center right away.

Directions

- apply liberally 15 minutes before sun exposure
- reapply:
  - after 40 minutes of swimming or sweating
  - immediately after towel drying
  - at least every 2 hours
- Sun Protection Measures.Spending time in the sun increases your risk of skin cancer and early skin aging. To decrease this risk, regularly use a sunscreen with a broad spectrum SPF value of 15 or higher and other sun protection measures including:
  - limit time in the sun, especially from 10 a.m.–2 p.m.
  - wear long-sleeved shirts, pants, hats, and sunglasses
- children under 6 months of age: ask a doctor

Other information

- protect the product in this container from excessive heat and direct sun

Inactive ingredients

water, C12-15 alkyl benzoate, caprylic/capric triglyceride, coco-caprylate, polyglyceryl-2 dipolyhydroxystearate, dicaprylyl carbonate, polyglyceryl-4 isostearate, cetyl dimethicone, glycerin, copernicia cerifera (carnauba) wax, cetyl alcohol, euphorbia cerifera (candelilla) wax, tapioca starch, calendula officinalis flower extract, chamomilla recutita (matricaria) flower extract, aloe barbadensis leaf juice, triethoxycaprylylsilane, tocopheryl acetate, magnesium sulfate, sodium chloride, silica dimethyl silylate, stearic acid, chlorphenesin, phenoxyethanol.

Questions or comments?

1.800.272.6663

Monday–Friday 6 a.m.–6 p.m. Pacific time

Distributed by
Arbonne International, LLC
Greenwood, IN 46143 USA

PRINCIPAL DISPLAY PANEL - 177 mL Tube Carton

ABC
ARBONNE BABY CARE®

SUNSCREEN
BROAD SPECTRUM SPF 30

WATER-RESISTANT
(40 Minutes)

6 fl. oz./177 mL